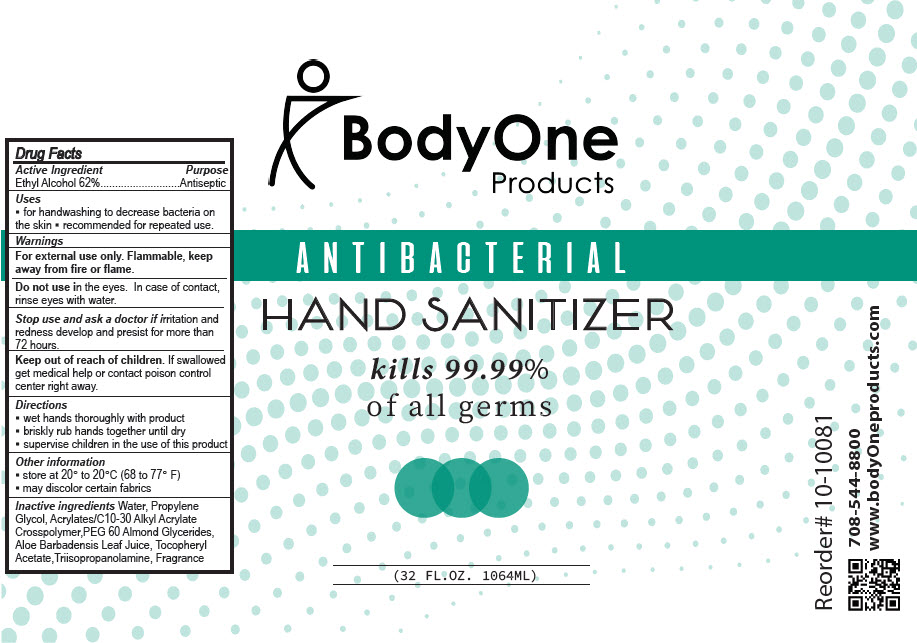 DRUG LABEL: Antibacterial Hand Sanitizer
NDC: 73563-080 | Form: GEL
Manufacturer: Body One Products , Inc.
Category: otc | Type: HUMAN OTC DRUG LABEL
Date: 20200807

ACTIVE INGREDIENTS: Alcohol 62 mL/100 mL
INACTIVE INGREDIENTS: Propylene Glycol; water; PEG-60 ALMOND GLYCERIDES; ALOE VERA LEAF; .ALPHA.-TOCOPHEROL ACETATE; TRIISOPROPANOLAMINE; CARBOMER INTERPOLYMER TYPE B (ALLYL PENTAERYTHRITOL CROSSLINKED)

Antibacterial Hand Sanitizer

Drug Facts

Active Ingredient

Ethyl Alcohol 62%

Purpose

Antiseptic

Uses

- for handwashing to decrease bacteria on the skin
- recommended for repeated use.

Warnings

For external use only. Flammable, keep away from fire or flame.

Do not use in the eyes. In case of contact, rinse eyes with water.

Stop use and ask a doctor if irritation and redness develop and presist for more than 72 hours.

Keep out of reach of children. If swallowed get medical help or contact poison control center right away.

Directions

- wet hands thoroughly with product
- briskly rub hands together until dry
- supervise children in the use of this product

Other information

- store at 20° to 20°C (68 to 77° F)
- may discolor certain fabrics

Inactive ingredients

Water, Propylene Glycol, Acrylates/C10-30 Alkyl Acrylate Crosspolymer,PEG 60 Almond Glycerides, Aloe Barbadensis Leaf Juice, Tocopheryl Acetate,Triisopropanolamine, Fragrance

PRINCIPAL DISPLAY PANEL - 1064 ML Bottle Label

BodyOne
Products

ANTIBACTERIAL
HAND SANITIZER

kills 99.99%
of all germs

(32 FL.OZ. 1064ML)